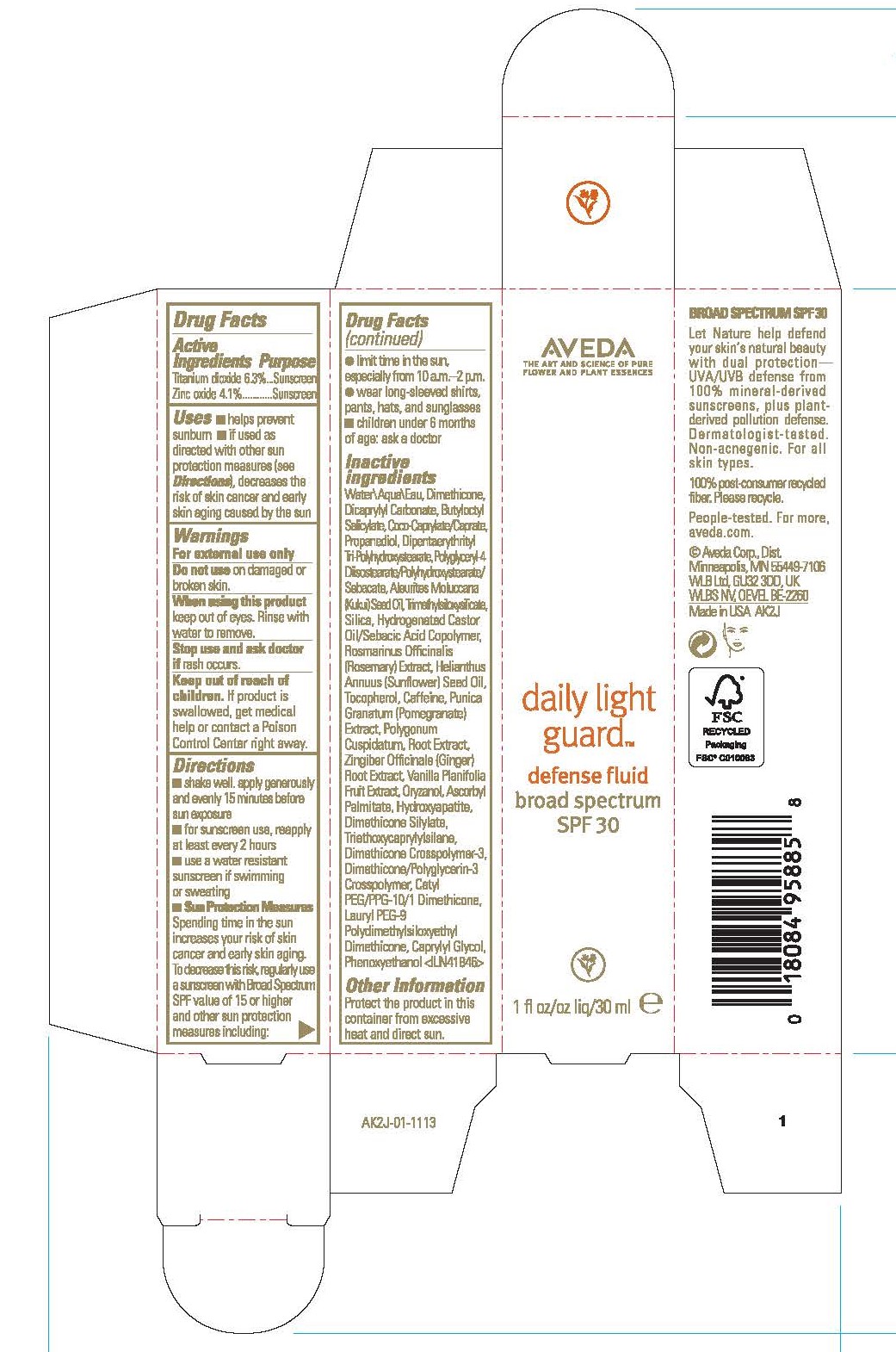 DRUG LABEL: DAILY LIGHT GUARD DEFENSE FLUID BROAD SPECTRUM SPF 30
NDC: 57677-063 | Form: LOTION
Manufacturer: Aveda Corporation
Category: otc | Type: HUMAN OTC DRUG LABEL
Date: 20241111

ACTIVE INGREDIENTS: TITANIUM DIOXIDE 63 mg/1 mL; ZINC OXIDE 41 mg/1 mL
INACTIVE INGREDIENTS: WATER; DIMETHICONE; DICAPRYLYL CARBONATE; BUTYLOCTYL SALICYLATE; COCOYL CAPRYLOCAPRATE; PROPANEDIOL; DIPENTAERYTHRITYL TRI-POLYHYDROXYSTEARATE; KUKUI NUT OIL; SILICON DIOXIDE; ROSEMARY; SUNFLOWER OIL; TOCOPHEROL; CAFFEINE; POMEGRANATE; REYNOUTRIA JAPONICA ROOT; GINGER; VANILLA BEAN; ORYZANOL; ASCORBYL PALMITATE; TRIBASIC CALCIUM PHOSPHATE; TRIETHOXYCAPRYLYLSILANE; LAURYL PEG-9 POLYDIMETHYLSILOXYETHYL DIMETHICONE; CAPRYLYL GLYCOL; PHENOXYETHANOL

DAILY LIGHT GUARD™ DEFENSE FLUID BROAD SPECTRUM SPF 30

Drug Facts

ACTIVE INGREDIENT

Active Ingredients | Purpose
Titanium dioxide 6.3% | Sunscreen
Zinc oxide 4.1% | Sunscreen

Uses

- helps prevent sunburn
- if used as directed with other sun protection measures (see Directions), decreases the risk of skin cancer and early skin aging caused by the sun

Warnings

For external use only

Do not use on damaged or broken skin.

When using this product keep out of eyes. Rinse with water to remove.

Stop use and ask doctor if rash occurs.

Keep out of reach of children. If product is swallowed, get medical help or contact a Poison Control Center right away.

Directions

- shake well. apply generously 15 minutes before sun exposure
- for sunscreen use, reapply at least every 2 hours
- use a water-resistant sunscreen if swimming or sweating
- Sun Protection Measures Spending time in the sun increases your risk of skin cancer and early skin aging. To decrease this risk, regularly use a sunscreen with Broad Spectrum SPF value of 15 or higher and other sun protection measures including:
  - limit time in the sun, especially from 10 a.m.–2 p.m.
  - wear long-sleeve shirts, pants, hats, and sunglasses
- children under 6 months of age: ask a doctor

Inactive ingredients

Water\Aqua\Eau, Dimethicone, Dicaprylyl Carbonate, Butyloctyl Salicylate, Coco-Caprylate/Caprate, Propanediol, Dipentaerythrityl Tri-Polyhydroxystearate, Polyglyceryl-4 Diisostearate/Polyhydroxystearate/Sebacate, Aleurites Moluccana (Kukui) Seed Oil, Trimethylsiloxysilicate, Silica, Hydrogenated Castor Oil/Sebacic Acid Copolymer, Rosmarinus Officinalis (Rosemary) Extract, Helianthus Annuus (Sunflower) Seed Oil, Tocopherol, Caffeine, Punica Granatum (Pomegranate) Extract, Polygonum Cuspidatum, Root Extract, Zingiber Officinale (Ginger) Root Extract, Vanilla Planifolia Fruit Extract, Oryzanol, Ascorbyl Palmitate, Hydroxyapatite, Dimethicone Silylate, Triethoxycaprylylsilane, Dimethicone Crosspolymer-3, Dimethicone/Polyglycerin-3 Crosspolymer, Cetyl PEG/PPG-10/1 Dimethicone, Lauryl PEG-9 Polydimethylsiloxyethyl Dimethicone, Caprylyl Glycol, Phenoxyethanol <ILN41846>

Other Information

Protect the product in this container from excessive heat and direct sun.

PRINCIPAL DISPLAY PANEL - 30 ml Bottle Carton

AVEDA
THE ART AND SCIENCE OF PURE
FLOWER AND PLANT ESSENCES

daily light
guard™

defense fluid
broad spectrum
SPF 30

1 fl oz/oz liq/30 ml e